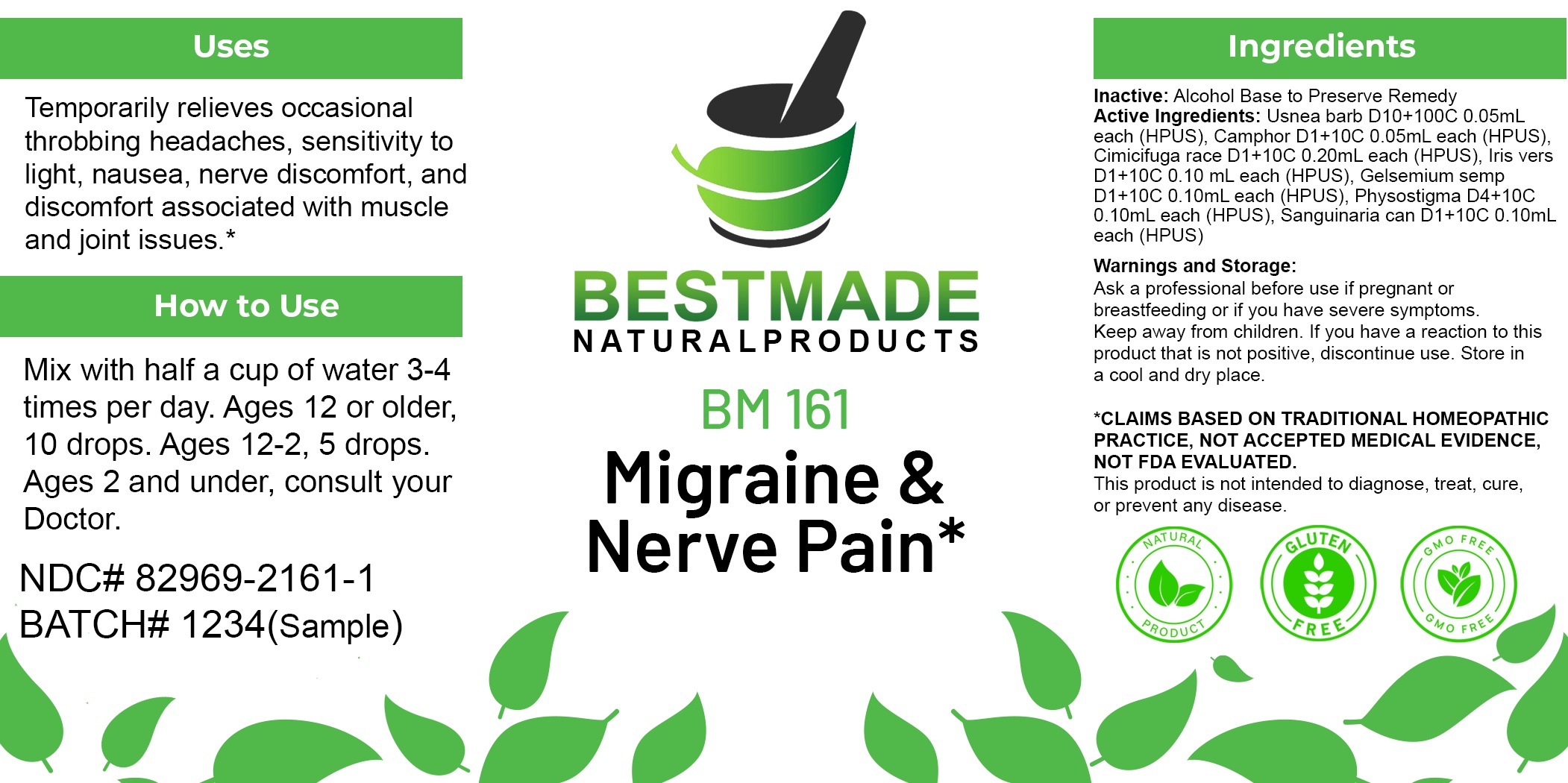 DRUG LABEL: Bestmade Natural Products BM161
NDC: 82969-2161 | Form: LIQUID
Manufacturer: Bestmade Natural Products
Category: homeopathic | Type: HUMAN OTC DRUG LABEL
Date: 20250218

ACTIVE INGREDIENTS: CAMPHOR (NATURAL) 30 [hp_C]/30 [hp_C]; SANGUINARIA CANADENSIS WHOLE 30 [hp_C]/30 [hp_C]; GELSEMIUM SEMPERVIRENS WHOLE 30 [hp_C]/30 [hp_C]; PHYSOSTIGMA VENENOSUM SEED 30 [hp_C]/30 [hp_C]; USNEA BARBATA 30 [hp_C]/30 [hp_C]; IRIS VERSICOLOR ROOT 30 [hp_C]/30 [hp_C]; BLACK COHOSH 30 [hp_C]/30 [hp_C]
INACTIVE INGREDIENTS: ALCOHOL 30 [hp_C]/30 [hp_C]

BM161

DOSAGE AND ADMINISTRATION

How to Use

Mix with half a cup of water 3-4 times per day. Ages 12 or older, 10 drops. Ages 12-2, 5 drops. Ages 2 and under, consult your Doctor.

Inactive:

Alcohol Base to Preserve Product

ACTIVE INGREDIENTS

Usnea barb D10+100C 0.05mL each (HPUS), Camphor D1+10C 0.05mL each (HPUS), Cimicifuga race D1+10C 0.20mL each (HPUS), Iris vers D1+10C 0.10 mL each (HPUS), Gelsemium semp D1+10C 0.10mL each (HPUS), Physostigma D4+10C 0.10mL each (HPUS), Sanguinaria can D1+10C 0.10mL each (HPUS)

Uses
Temporarily relieves occasional throbbing headaches, sensitivity to light, nausea, nerve discomfort, and discomfort associated with muscle and joint issues.*

Uses
Temporarily relieves occasional throbbing headaches, sensitivity to light, nausea, nerve discomfort, and discomfort associated with muscle and joint issues.*

KEEP OUT OF REACH OF CHILDREN

Warnings and Storage:

Ask a professional before use if pregnant or breastfeeding or if you have severe symptoms.

Keep away from children. If you have a reaction to this product that is not positive, discontinue use. Store in a cool and dry place

*CLAIMS BASED ON TRADITIONAL HOMEOPATHIC PRACTICE, NOT ACCEPTED MEDICAL EVIDENCE NOT FDA EVALUATED.
This product is not intended to diagnose, treat, cure, or prevent any disease.

Warnings and Storage:

Ask a professional before use if pregnant or breastfeeding or if you have severe symptoms.

Keep away from children. If you have a reaction to this product that is not positive, discontinue use. Store in a cool and dry place

*CLAIMS BASED ON TRADITIONAL HOMEOPATHIC PRACTICE, NOT ACCEPTED MEDICAL EVIDENCE NOT FDA EVALUATED.
This product is not intended to diagnose, treat, cure, or prevent any disease.

Entire package label